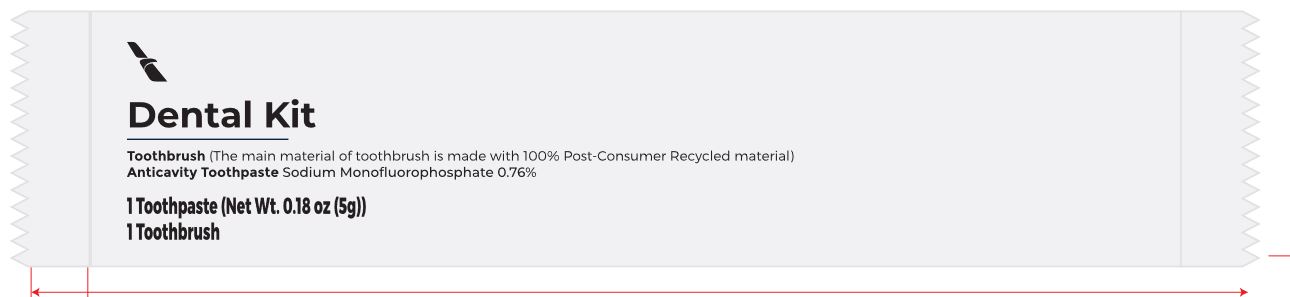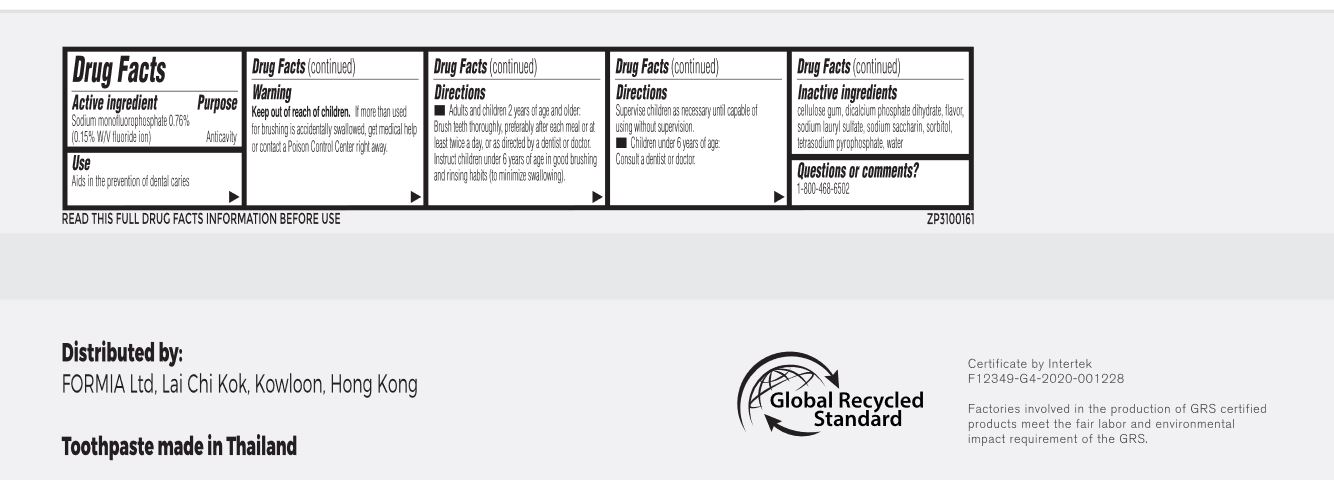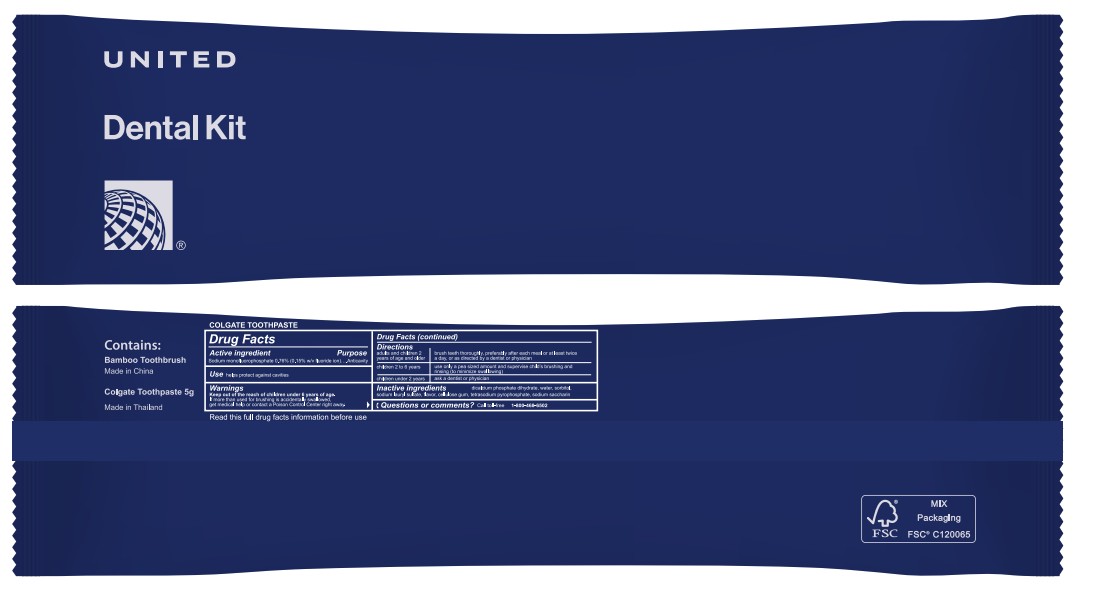 DRUG LABEL: Colgate 5g and Toothbrush Dental Kit
NDC: 79940-004 | Form: KIT | Route: DENTAL
Manufacturer: FORMIA LIMITED
Category: otc | Type: HUMAN OTC DRUG LABEL
Date: 20260128

ACTIVE INGREDIENTS: SODIUM MONOFLUOROPHOSPHATE 1.5 mg/1 g
INACTIVE INGREDIENTS: CARBOXYMETHYLCELLULOSE SODIUM, UNSPECIFIED; DIBASIC CALCIUM PHOSPHATE DIHYDRATE; METHYL SALICYLATE; SODIUM LAURYL SULFATE; SACCHARIN SODIUM; SORBITOL; SODIUM PYROPHOSPHATE; WATER

Colgate 5g Toothpaste and Toothbrush Dental Kit

Active ingredient

Sodium monofluorophosphate 0.76% (0.15% w/v fluoride ion)

Purpose

Anticavity

Use

Aids in the prevention of dental caries

Warning

Keep out of reach of children.

If more than used for brushing is accidentally swallowed, get medical help or contact a Poison Control Center right away.

Directions

- Adults and children 2 years of age and older: Brush teeth thoroughly, preferably after each meal or at least twice a day, or as directed by a dentist or doctor. Instruct children under 6 years of age in good brushing and rinising habits (to minimize swallowing). Supervuse children as necessary until capable of using without supervision.

- Children under 6 years of age: Consult a dentist or doctor.

Inactive ingredients

cellulose gum, dicalcium phosphate dihydrate, flavor, sodium lauryl sulfate, sodium saccharin, sorbitol, tetrasodium pyrophosphate, water

Questions or comments?

1-800-468-6502